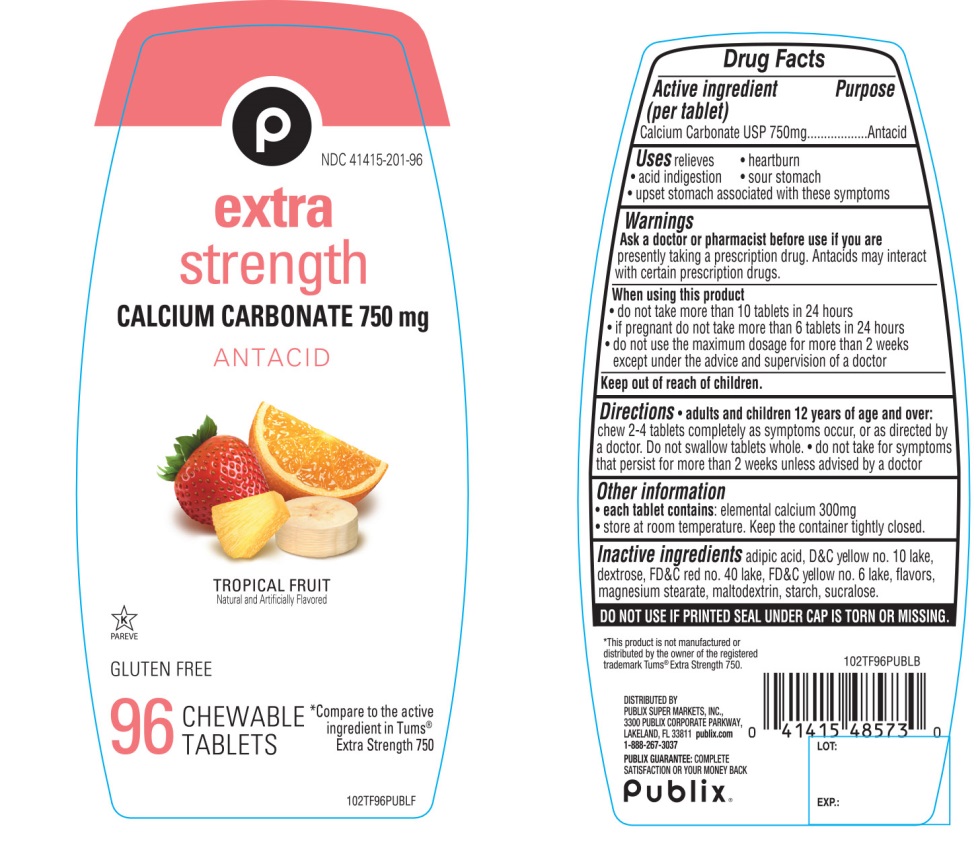 DRUG LABEL: Publix Extra Strength

NDC: 41415-201 | Form: TABLET, CHEWABLE
Manufacturer: PUBLIX SUPER MARKETS, INC
Category: otc | Type: HUMAN OTC DRUG LABEL
Date: 20251028

ACTIVE INGREDIENTS: CALCIUM CARBONATE 750 mg/1 1
INACTIVE INGREDIENTS: ADIPIC ACID; D&C YELLOW NO. 10; DEXTROSE, UNSPECIFIED FORM; FD&C RED NO. 40; FD&C YELLOW NO. 6; MAGNESIUM STEARATE; MALTODEXTRIN; STARCH, CORN; SUCRALOSE

Publix Extra Strength Tropical Fruit Antacid 96 Tabs Drug Facts

Active ingredient (per tablet)

Calcium Carbonate USP 750mg

Purpose

Antacid

Uses

relieves

- heartburn
- acid indigestion
- sour stomach
- upset stomach associated with these symptoms

Warnings

Ask a doctor or pharmacist before use if you are

presently taking a prescription drug. Antacids may interact with certain prescription drug.

When using this product

- do not take more than 10 tablets in 24 hours
- if pregnant do not take more than 6 tablets in 24 hours
- do not use the maximum dosage for more than 2 weeks except under the advice and supervision of a doctor

Directions

- adults and children 12 years of age and over:chew 2-4 tablets as symptoms occur, or as directed by a doctor. Do not swallow tablets whole.
- do not take for symptoms that persist for more than 2 weeks unless advised by a doctor

Other information

- each tablet contains: elemental calcium 300mg
- Store at room temperature. Keep the container tightly closed.

Inactive ingredients

adipic acid, D&C yellow # 10 lake, dextrose, FD&C red # 40 lake, FD&C yellow # 6 lake, flavors, magnesium stearate, maltodextrin, starch, sucralose.

Questions or comments?

1-888-267-3037

SAFETY SEALED: DO NOT USE IF PRINTED SEAL UNDER CAP IS TORN OR MISSING.

Principal Display Panel

* Compare to the active ingredient in Tums® Extra Strength Tropical Fruit Flavor

Publix®

NDC# 41415-201-96

Extra Strength

Antacid Tablets

CALCIUM CARBONATE 750 MG/ANTACID

TROPICAL FRUIT

Natural and Artificially Flavored

96 CHEWABLE TABLETS

GLUTEN FREE

K PAREVE

DISTRIBUTED BY:

PUBLIX SUPER MARKETS, INC.,

3300 PUBLIX CORPORATE PARKWAY,

LAKELAND, FL 33811 publix.com

1-888-267-3037

PUBLIX GUARANTEE: COMPLETE SATISFACTION OR YOUR MONEY BACK

*This product is not manufactured or distributed by GlaxoSmithKline LLC, owner of the registered trademark Tums®Extra Strength.